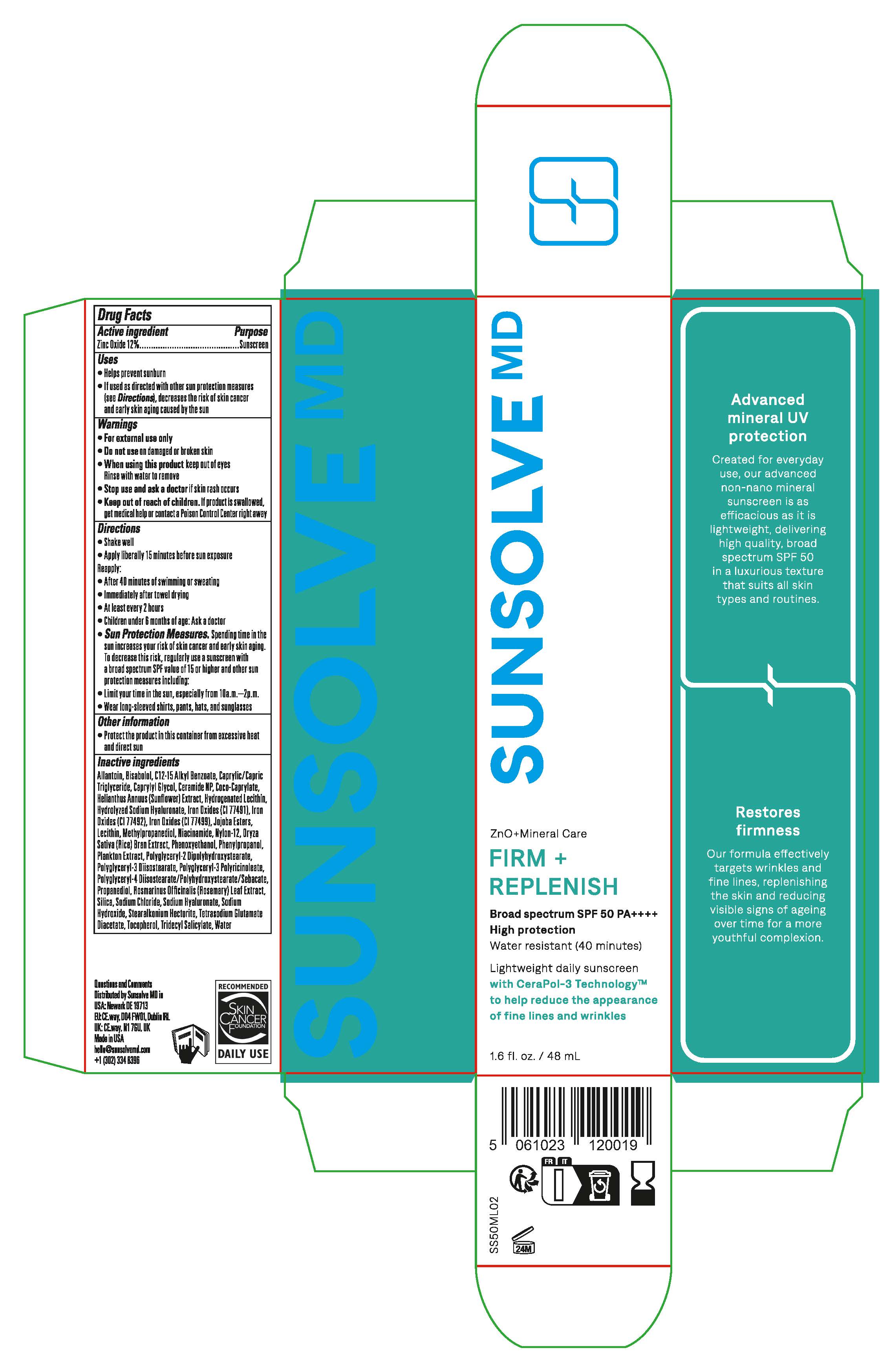 DRUG LABEL: Sunsolve MD Firm and Replenish
NDC: 84878-199 | Form: LOTION
Manufacturer: Sunsolve MD Inc
Category: otc | Type: HUMAN OTC DRUG LABEL
Date: 20251114

ACTIVE INGREDIENTS: ZINC OXIDE 132 mg/1 mL
INACTIVE INGREDIENTS: SODIUM HYALURONATE; TOCOPHEROL; PHENOXYETHANOL; FERRIC OXIDE YELLOW; CERAMIDE NP; JOJOBA OIL; ORYZA SATIVA WHOLE; TRIDECYL SALICYLATE; SILICON DIOXIDE; CAPRYLYL GLYCOL; COCO-CAPRYLATE; NYLON-12; PHENYLPROPANOL; HELIANTHUS ANNUUS FLOWERING TOP; LECITHIN, SOYBEAN; METHYLPROPANEDIOL; POLYGLYCERYL-2 DIPOLYHYDROXYSTEARATE; ALLANTOIN; ALKYL (C12-15) BENZOATE; ROSMARINUS OFFICINALIS FLOWER; .ALPHA.-BISABOLOL, (+)-; SODIUM HYDROXIDE; WATER; NIACINAMIDE; TETRASODIUM GLUTAMATE DIACETATE; PROPANEDIOL; POLYGLYCERYL-4 DIISOSTEARATE/POLYHYDROXYSTEARATE/SEBACATE; STEARALKONIUM HECTORITE; POLYGLYCERYL-3 DIISOSTEARATE; CAPRYLIC/CAPRIC TRIGLYCERIDE; FERROSOFERRIC OXIDE; SODIUM CHLORIDE; FERRIC OXIDE RED

Sunsolve MD Firm and Replenish